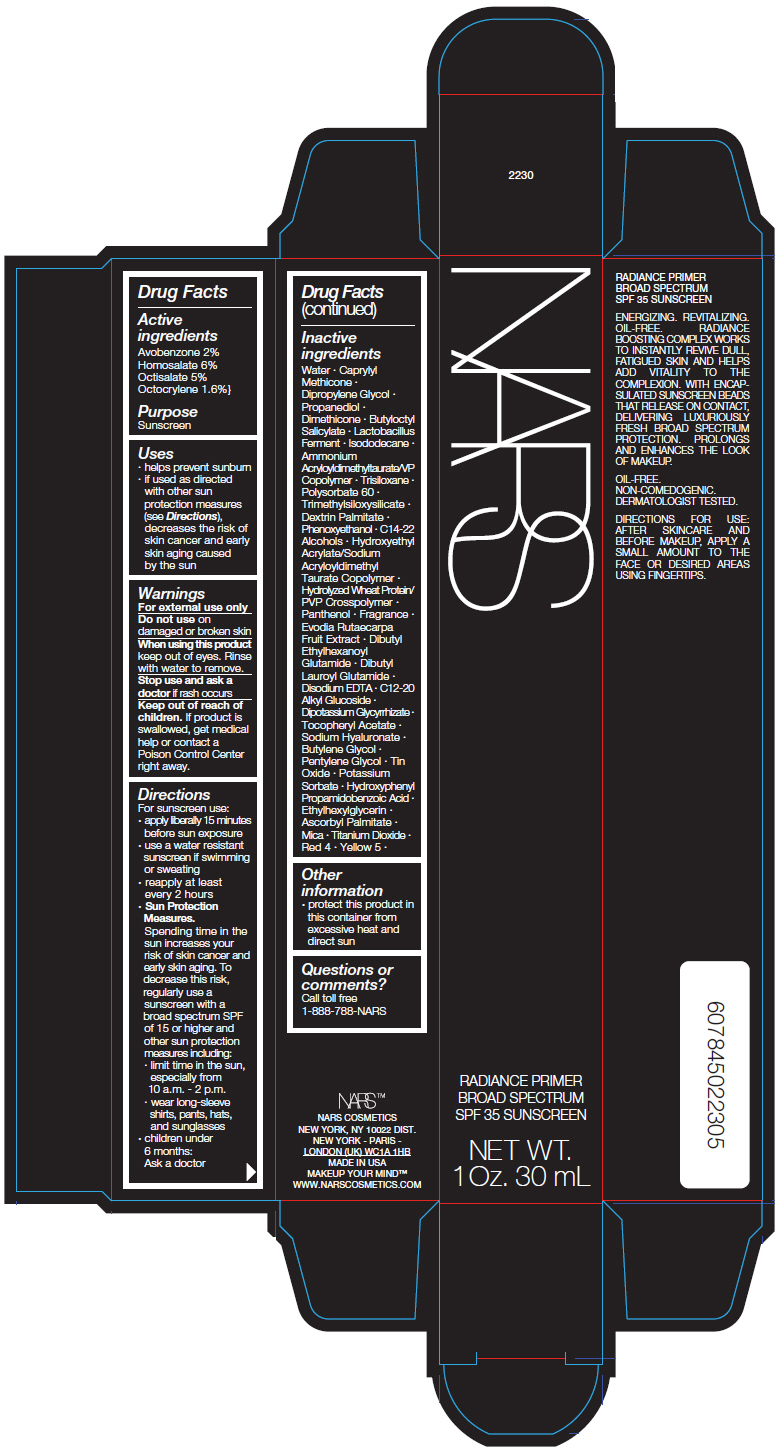 DRUG LABEL: NARS RADIANCE PRIMER
NDC: 13734-158 | Form: CREAM
Manufacturer: NARS Cosmetics
Category: otc | Type: HUMAN OTC DRUG LABEL
Date: 20181126

ACTIVE INGREDIENTS: AVOBENZONE 602.4 mg/30 mL; HOMOSALATE 1807.2 mg/30 mL; OCTISALATE 1506 mg/30 mL; OCTOCRYLENE 481.9 mg/30 mL
INACTIVE INGREDIENTS: WATER; CAPRYLYL TRISILOXANE; DIPROPYLENE GLYCOL; PROPANEDIOL; DIMETHICONE; BUTYLOCTYL SALICYLATE; MICA; LIMOSILACTOBACILLUS REUTERI; TITANIUM DIOXIDE; ISODODECANE; AMMONIUM ACRYLOYLDIMETHYLTAURATE/VP COPOLYMER; TRISILOXANE; POLYSORBATE 60; TRIMETHYLSILOXYSILICATE (M/Q 0.6-0.8); DEXTRIN PALMITATE (CORN; 20000 MW); PHENOXYETHANOL; C14-22 ALCOHOLS; HYDROXYETHYL ACRYLATE/SODIUM ACRYLOYLDIMETHYL TAURATE COPOLYMER (100000 MPA.S AT 1.5%); PANTHENOL; TETRADIUM RUTICARPUM FRUIT; DIBUTYL ETHYLHEXANOYL GLUTAMIDE; DIBUTYL LAUROYL GLUTAMIDE; EDETATE DISODIUM; .ALPHA.-TOCOPHEROL ACETATE, DL-; C12-20 ALKYL GLUCOSIDE; GLYCYRRHIZINATE DIPOTASSIUM; HYALURONATE SODIUM; PENTYLENE GLYCOL; BUTYLENE GLYCOL; STANNIC OXIDE; POTASSIUM SORBATE; FD&C RED NO. 4; FD&C YELLOW NO. 5; HYDROXYPHENYL PROPAMIDOBENZOIC ACID; ETHYLHEXYLGLYCERIN; ASCORBYL PALMITATE

NARS RADIANCE PRIMER

Drug Facts

Active ingredients

Avobenzone 2%
Homosalate 6%
Octisalate 5%
Octocrylene 1.6%}

Purpose

Sunscreen

Uses

- helps prevent sunburn
- if used as directed with other sun protection measures (see Directions), decreases the risk of skin cancer and early skin aging caused by the sun

Warnings

For external use only

Do not use on damaged or broken skin

When using this product keep out of eyes. Rinse with water to remove.

Stop use and ask a doctor if rash occurs

Keep out of reach of children. If product is swallowed, get medical help or contact a Poison Control Center right away.

Directions

For sunscreen use:

- apply liberally 15 minutes before sun exposure
- use a water resistant sunscreen if swimming or sweating
- reapply at least every 2 hours
- Sun Protection Measures.
  Spending time in the sun increases your risk of skin cancer and early skin aging. To decrease this risk, regularly use a sunscreen with a broad spectrum SPF of 15 or higher and other sun protection measures including:
  - limit time in the sun, especially from 10 a.m. - 2 p.m.
  - wear long-sleeve shirts, pants, hats, and sunglasses
- children under 6 months: Ask a doctor

Inactive ingredients

Water ∙ Caprylyl Methicone ∙ Dipropylene Glycol ∙ Propanediol ∙ Dimethicone ∙ Butyloctyl Salicylate ∙ Lactobacillus Ferment ∙ Isododecane ∙ Ammonium Acryloyldimethyltaurate/VP Copolymer ∙ Trisiloxane ∙ Polysorbate 60 ∙ Trimethylsiloxysilicate ∙ Dextrin Palmitate ∙ Phenoxyethanol ∙ C14-22 Alcohols ∙ Hydroxyethyl Acrylate/Sodium Acryloyldimethyl Taurate Copolymer ∙ Hydrolyzed Wheat Protein/PVP Crosspolymer ∙ Panthenol ∙ Fragrance ∙ Evodia Rutaecarpa Fruit Extract ∙ Dibutyl Ethylhexanoyl Glutamide ∙ Dibutyl Lauroyl Glutamide ∙ Disodium EDTA ∙ C12-20 Alkyl Glucoside ∙ Dipotassium Glycyrrhizate ∙ Tocopheryl Acetate ∙ Sodium Hyaluronate ∙ Butylene Glycol ∙ Pentylene Glycol ∙ Tin Oxide ∙ Potassium Sorbate ∙ Hydroxyphenyl Propamidobenzoic Acid ∙ Ethylhexylglycerin ∙ Ascorbyl Palmitate ∙ Mica ∙ Titanium Dioxide ∙ Red 4 ∙ Yellow 5 ∙

Other information

- protect this product in this container from excessive heat and direct sun

Questions or comments?

Call toll free 1-888-788-NARS

PRINCIPAL DISPLAY PANEL - 30 mL Tube Carton

NARS

RADIANCE PRIMER
BROAD SPECTRUM
SPF 35 SUNSCREEN

NET WT.
1 Oz. 30 mL